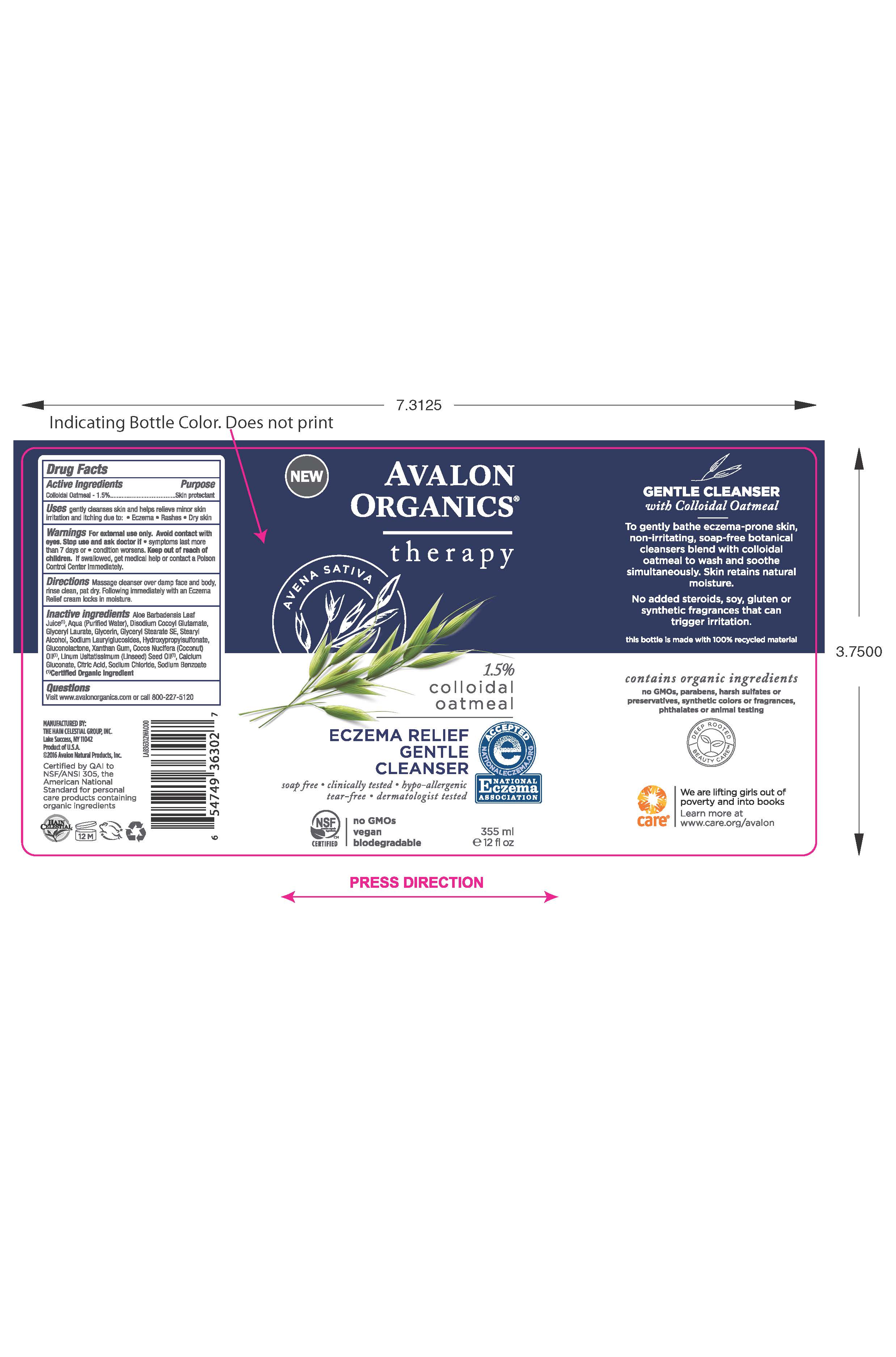 DRUG LABEL: AV3630200 Avalon Organics Eczema Relief Gentle Cleanser
NDC: 61995-1302 | Form: LOTION
Manufacturer: The Hain Celestial Group, Inc.
Category: otc | Type: HUMAN OTC DRUG LABEL
Date: 20210205

ACTIVE INGREDIENTS: OATMEAL 1.5 g/100 g
INACTIVE INGREDIENTS: CALCIUM GLUCONATE; CITRIC ACID MONOHYDRATE; COCONUT OIL; ALOE VERA LEAF; GLYCERIN; WATER; GLYCERYL STEARATE SE; XANTHAN GUM; SODIUM BENZOATE; DISODIUM COCOYL GLUTAMATE; GLUCONOLACTONE; SODIUM CHLORIDE; LINSEED OIL; GLYCERYL LAURATE; STEARYL ALCOHOL

AV3630200 Avalon Organics Eczema Relief Gentle Cleanser

Active Ingredient

Colloidal Oatmeal - 1.5%

DOSAGE AND ADMINISTRATION

Massage cleanser over damp face and body, rinse clean, pat dry. Following immediately with an Eczema Relief cream locks in moisture.

PURPOSE

Skin Protectant

WARNINGS

For external use only. Avoid contacts with eyes. Stop use and ask a doctor if symptoms last more than 7 days or condition worsens.

Keep out of reach of children. If swallowed get medical help or contact Poison Center immediately.

INACTIVE INGREDIENT

Water, Aloe Barbadensis Leaf Juice(1), Disodium Cocoyl Glutamate, Glyceryl Laurate, Glycerin, Glyceryl Stearate SE, Stearyl Alcohol, Cocos Nucifera (Coconut) Oil (1), Sodium Laurylglucosides Hydroxypropylsulfonate, Xanthan Gum, Linum Usatatissimum (Linseed) Seed Oil (1), Gluconolactone, Calcium Gluconate, Citric Acid, Sodium Chloride, Sodium Benzoate.

(1) Certified Organicf Ingredient

INDICATIONS AND USAGE

Gentle cleanses skin and helps relieve minor skin irritation and iching due to eczema, rashes, dry skin.